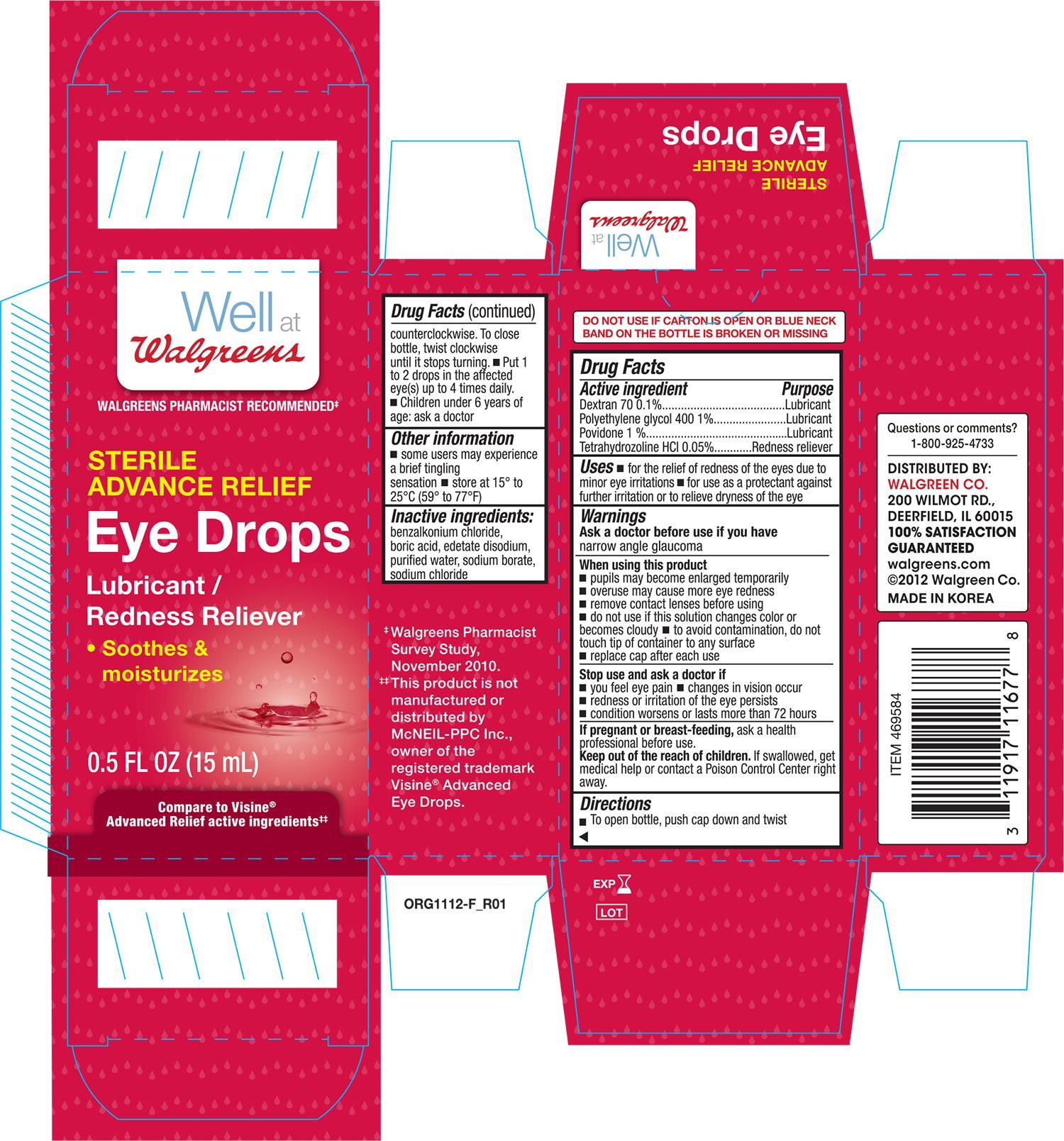 DRUG LABEL: Walgreens Sterile Advance Relief Eye Drops
NDC: 0363-1677 | Form: SOLUTION/ DROPS
Manufacturer: Walgreen Company
Category: otc | Type: HUMAN OTC DRUG LABEL
Date: 20141125

ACTIVE INGREDIENTS: DEXTRAN 70 .001 mg/1 mg; POLYETHYLENE GLYCOL 400 .01 mg/1 mg; POVIDONE .01 mg/1 mg; TETRAHYDROZOLINE HYDROCHLORIDE .0005 mg/1 mg
INACTIVE INGREDIENTS: BENZALKONIUM CHLORIDE; BORIC ACID; EDETATE DISODIUM; WATER; SODIUM BORATE; SODIUM CHLORIDE

Active Ingredients Purpose

Dextran 70 0.1%................................................ Lubricant

Polyethylene glycol 400 1%.................................. Lubricant

Tetrahydrozoline HCI 0.05%................................. Redness Reliever

Uses

- for the relief of redness of the eyes due to minor eye irritations
- for use as a protection against further irritation or to relieve dryness of the eye

Warnings
Ask a doctor before use if you have narrow angle glaucoma

When using this product

- pupils may become enlarged temporarily
- overuse may cause more eye redness
- remove contact lenses before using
- do not use if this solution changes color or becomes cloudy
- to avoid contamination, do not touch tip of container to any surface
- replace cap after each use

Stop use and ask a doctor if

- you feel eye pain
- changes in vision occur
- redness or irritation of the eye persists
- condition worsens or lasts more than 72 hours

PREGNANCY OR BREAST FEEDING

If pregnant or breast feeding, ask a health professional before use

Keep out of the reach of children.

If swallowed, get medical help or contact a Poision Control Center right away

Directions

- To open bottle, push cap down and twist counter-clockwise. To close bottle, twist clockwise until it stops turning
- put 1 to 2 drops in the affected eye(s) up to 4 times daily
- children under 6 years of age: ask a doctor

Other Information

- some users may experience a brief tangling sensation
- store at 15° to 25°C (59° to 77°F)

Inactive Ingredients:

benzalkonium chloride, boric acid, edetate disodium, purified water, sodium borate, and sodium chloride

DOSAGE AND ADMINISTRATION

DISTRIBUTED BY:

WALGREEN CO.

200 WILMOT RD.

DEERFIELD, IL 60015

Made in Korea